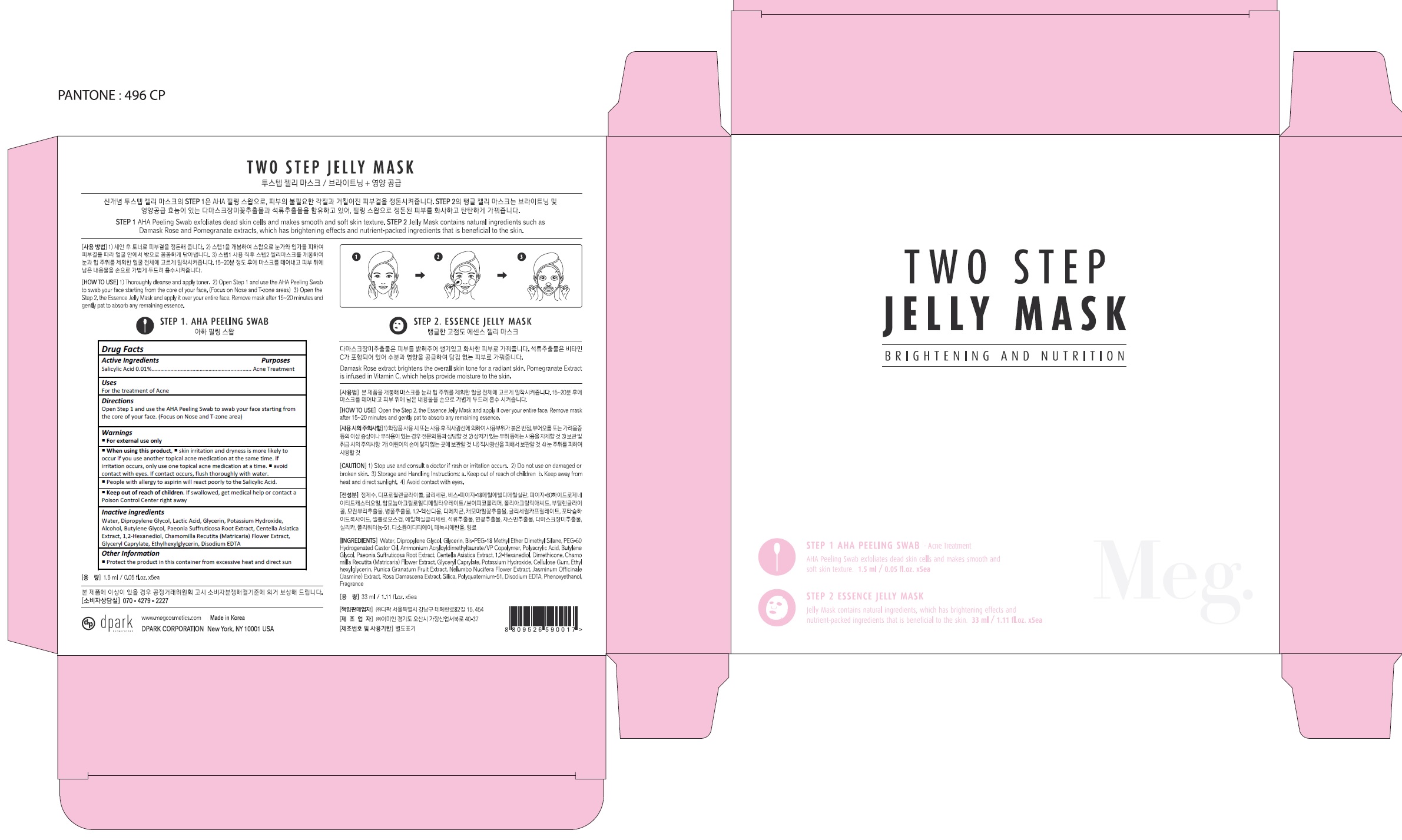 DRUG LABEL: Two Step Jelly Mask - Brightening and Nutrition
NDC: 73321-001 | Form: LIQUID
Manufacturer: Dpark Corporation
Category: otc | Type: HUMAN OTC DRUG LABEL
Date: 20190827

ACTIVE INGREDIENTS: SALICYLIC ACID 0.1 mg/1 mL
INACTIVE INGREDIENTS: WATER; DIPROPYLENE GLYCOL; LACTIC ACID, UNSPECIFIED FORM; GLYCERIN; POTASSIUM HYDROXIDE; ALCOHOL; BUTYLENE GLYCOL; PAEONIA X SUFFRUTICOSA ROOT; CENTELLA ASIATICA; 1,2-HEXANEDIOL; CHAMOMILE; GLYCERYL MONOCAPRYLATE; ETHYLHEXYLGLYCERIN; EDETATE DISODIUM ANHYDROUS

73321-001_Two Step Jelly Mask - Brightening and Nutrition

ACTIVE INGREDIENT

Salicylic Acid 0.01%

PURPOSE

Acne Treatment

INDICATIONS AND USAGE

For the treatment of Acne

DOSAGE AND ADMINISTRATION

Open Step 1 and use the AHA Peeling Swab to swab your face starting from the core of your face. (Focus on Nose and T-zone area)

WARNINGS

For external use only
When using this product, skin irritation and dryness is more likely to occur if you use another topical acne medication at the same time. If irritation occurs, only use one topical acne medication at a time.

Avoid contact with eyes. If contact occurs, flush thoroughly with water.
People with allergy to aspirin will react poorly to the Salicylic Acid.

KEEP OUT OF REACH OF CHILDREN

Keep out of reach of the children. If product is swallowed, get medical help or contact a poison control center right away.

INACTIVE INGREDIENT

Water, Dipropylene Glycol, Lactic Acid, Glycerin, Potassium Hydroxide, Alcohol, Butylene Glycol, Paeonia Suffruticosa Root Extract, Centella Asiatica Extract, 1,2-Hexanediol, Chamomilla Recutita (Matricaria) Flower Extract, Glyceryl Caprylate, Ethylhexylglycerin, Disodium EDTA